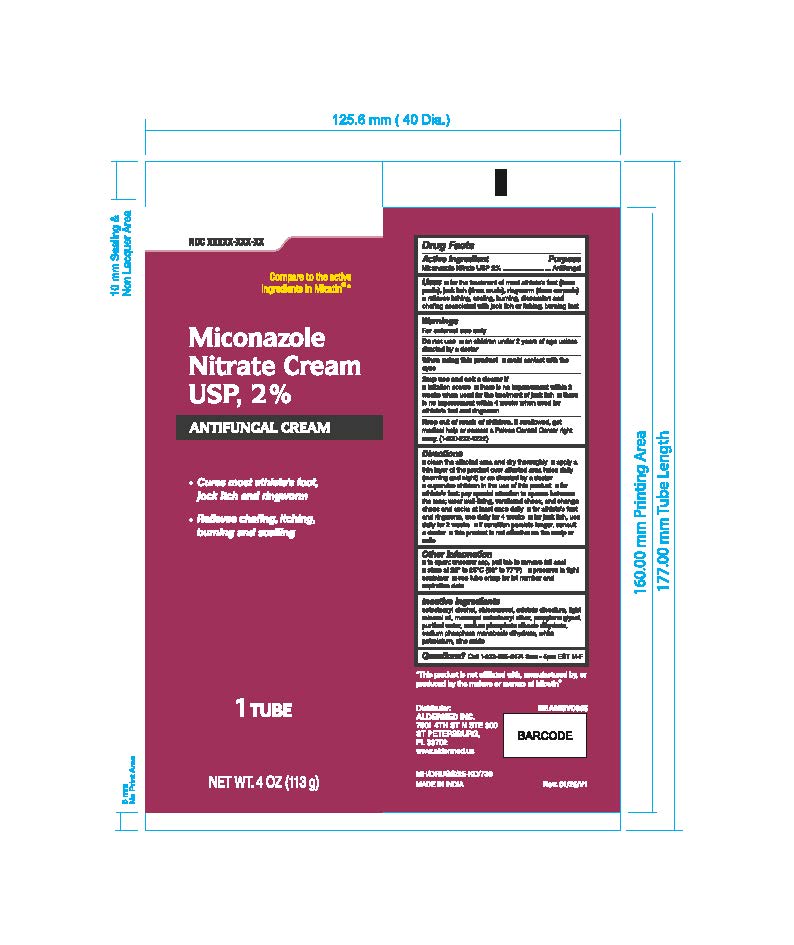 DRUG LABEL: Miconazole Cream
NDC: 87236-013 | Form: CREAM
Manufacturer: Aldermed Inc.
Category: otc | Type: HUMAN OTC DRUG LABEL
Date: 20260210

ACTIVE INGREDIENTS: MICONAZOLE NITRATE 2 g/100 g
INACTIVE INGREDIENTS: CHLOROCRESOL; WHITE PETROLATUM; ZINC OXIDE; SODIUM PHOSPHATE DIBASIC DIHYDRATE; LIGHT MINERAL OIL; CETEARETH-12; EDETATE DISODIUM; PROPYLENE GLYCOL; WATER; SODIUM PHOSPHATE, MONOBASIC, DIHYDRATE; CETOSTEARYL ALCOHOL

Miconazole Cream

Active ingredient

Miconazole Nitrate USP 2.0%

Purpose

Antifungal

Uses

- for the treatment of most athlete’s foot (tinea pedis), jock itch (tinea cruris), ringworm (tinea corporis)
- relieves itching, scaling, cracking, burning, discomfort and chafing associated with jock itching, burning feet irritation,

Warnings

For external use only

Do not use

- on children under 2 years of age unless directed by doctor

When using this product

- avoid contact with the eyes

Stop use and ask a doctor

■ irritation oc:curs

■ there is no improvement within 2 weeks when used for the treatment of jock itch
■ there is no improvement within 4 weeks when used for athlete's foot and ringworm

Keep out of reach of children.

If swallowed, get medical help or contact a Poison Control Center right away (1-800-222-1222)

Directions

■ clean the affected area and dry thoroughly

■ apply a thin layer of the product over affected area twice daily (morning and night) or as directed by a doctor
■ supervise children in the use of this product

■ for athlete's foot: pay special attention to spaces between the toes; wear well-fitting, ventilated shoes, and change shoes and socks at least once daily

■ for athlete's foot and ringworm, use daily for 4 weeks

■ for jock itch, use daily for 2 weeks

■ if condition persists longer, consult a doctor

■ this product is not effective on the scalp or nails

Other information

■ to open: unscrew cap, pull tab to remove foil seal

■ store at 20° to 25°C (68° to 77°F)

■preserve in tight container

■ see tube crimp for lot number and expiration date

Inactive ingredients

cetostearyl alcohol, chlorocresol, edetate disodium, light mineral oil, macrogol cetostearyl ether, propylene glycol, purified water, sodium phosphate dibasic dihydrate, sodium phosphate monobasic dihydrate, white petrolatum, zinc oxide.

Questions?

Call 1-833-605-8474 9am-5pm EST M-F